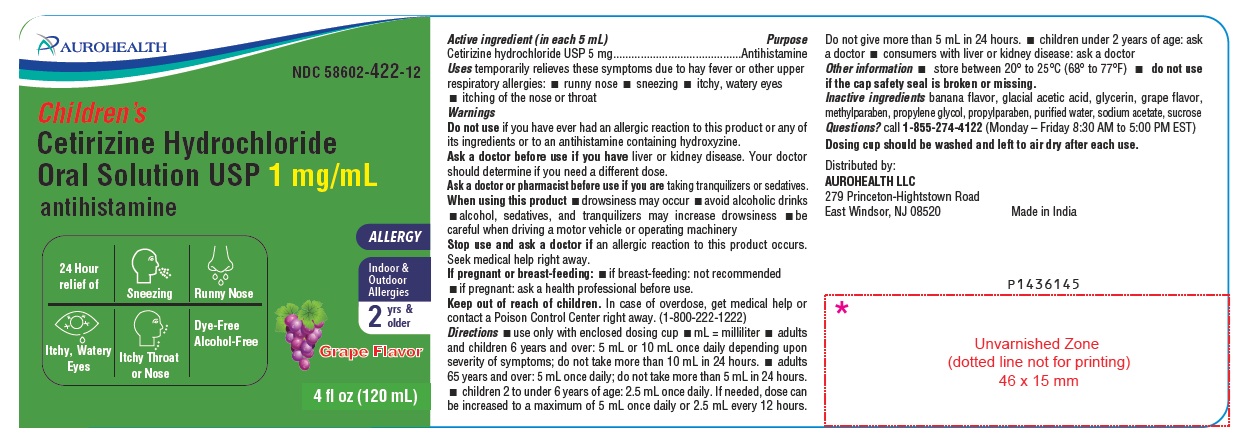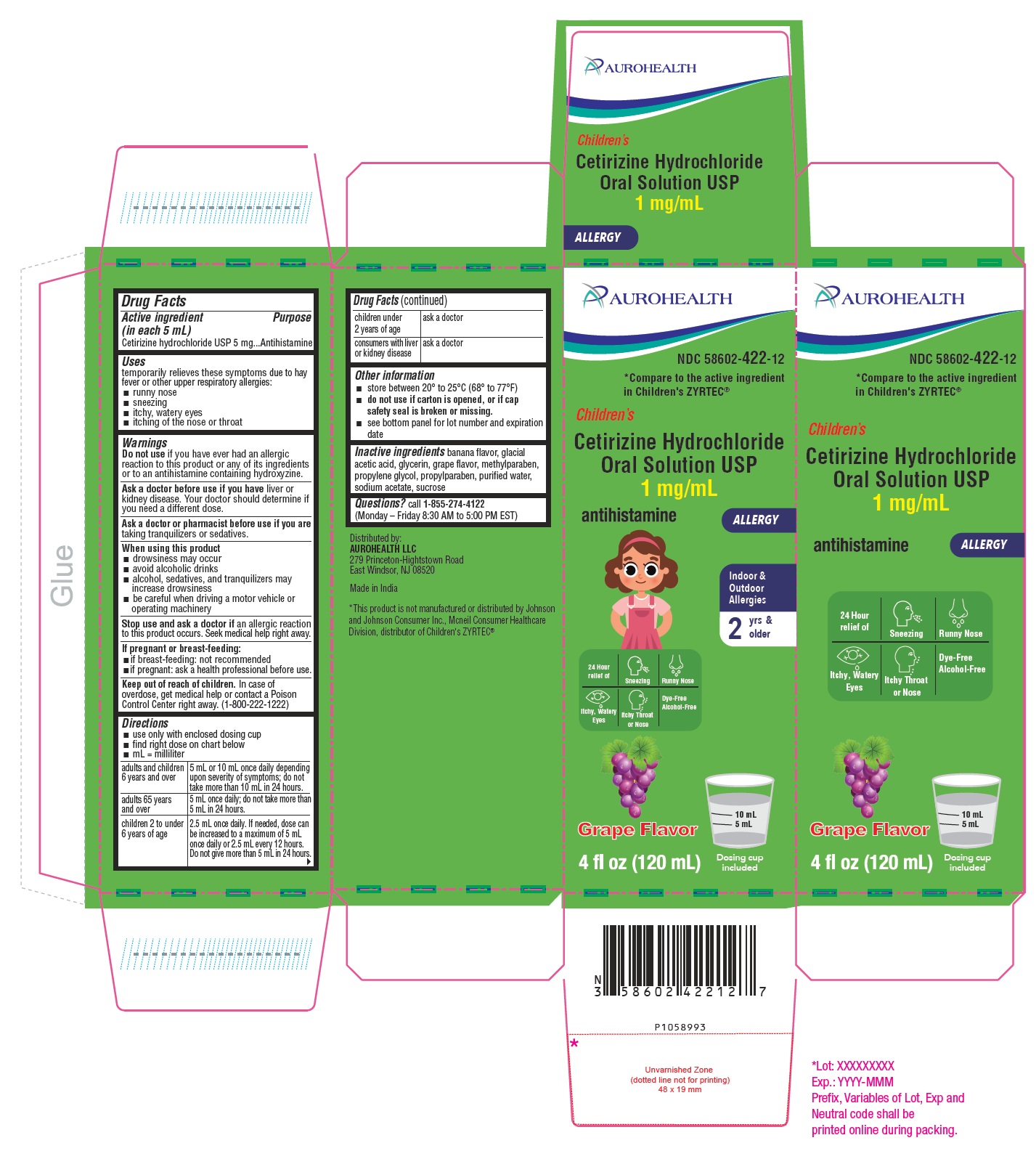 DRUG LABEL: Childrens Allergy Relief
NDC: 58602-422 | Form: SOLUTION
Manufacturer: Aurohealth LLC
Category: otc | Type: Human OTC Drug Label
Date: 20251209

ACTIVE INGREDIENTS: CETIRIZINE HYDROCHLORIDE 1 mg/1 mL
INACTIVE INGREDIENTS: ACETIC ACID; GLYCERIN; METHYLPARABEN; PROPYLENE GLYCOL; PROPYLPARABEN; WATER; SODIUM ACETATE; SUCROSE

Drug Facts

Active ingredient (in each 5 mL)

Cetirizine hydrochloride USP 5 mg

Purpose

Antihistamine

Uses

temporarily relieves these symptoms due to hay fever or other upper respiratory allergies:

- runny nose
- sneezing
- itchy, watery eyes
- itching of the nose or throat

Warnings

Do not use

if you have ever had an allergic reaction to this product or any of its ingredients or to an antihistamine containing hydroxyzine.

Ask a doctor before use if you have

liver or kidney disease. Your doctor should determine if you need a different dose.

Ask a doctor or pharmacist before use if you are

taking tranquilizers or sedatives.

When using this product

- drowsiness may occur
- avoid alcoholic drinks
- alcohol, sedatives, and tranquilizers may increase drowsiness
- be careful when driving a motor vehicle or operating machinery.

Stop use and ask a doctor if

an allergic reaction to this product occurs. Seek medical help right away.

If pregnant or breast-feeding:

- If breast-feeding: not recommended
- If pregnant: ask a health professional before use.

Keep out of reach of children.

In case of overdose, get medical help or contact a Poison Control Center right away. (1-800-222-1222)

Directions

- use only with enclosed dosing cup
- find right dose on chart below
- mL = milliliter

adults and children 6 years and over | 5 mL or 10 mL once daily depending upon severity of symptoms; do not take more than 10 mL in 24 hours.
adults 65 years and over | 5 mL once daily; do not take more than 5 mL in 24 hours.
children 2 to under 6 years of age | 2.5 mL once daily. If needed, dose can be increased to a maximum of 5 mL once daily or 2.5 mL every 12 hours. Do not give more than 5 mL in 24 hours.
children under 2 years of age | ask a doctor
consumers with liver or kidney disease | ask a doctor

Other information

- store between 20° to 25°C (68° to 77°F)
- do not use if carton is opened, or if cap safety seal is broken or missing.
- see bottom panel for lot number and expiration date

Inactive ingredients

banana flavor, glacial acetic acid, glycerin, grape flavor, methylparaben, propylene glycol, propylparaben, purified water, sodium acetate, sucrose

Questions?

call 1-855-274-4122
(Monday – Friday 8:30 AM to 5:00 PM EST)
Distributed by:
AUROHEALTH LLC
279 Princeton-Hightstown Road
East Windsor, NJ 08520
Made in India

PACKAGE LABEL-PRINCIPAL DISPLAY PANEL - 1 mg/mL (120 mL Bottle)

AUROHEALTH
NDC 58602-422-12
Children's
Cetirizine Hydrochloride
Oral Solution USP 1 mg/mL
antihistamine
24 Hour
relief of Sneezing Runny Nose

Itchy, Watery Itchy Throat Dye-Free
Eyes or Nose Alcohol-Free

ALLERGY
Indoor &
Outdoor
Allergies

2 yrs &
older
Grape Flavor
4 fl oz (120 mL)

PACKAGE LABEL-PRINCIPAL DISPLAY PANEL - 1 mg/mL Carton (120 mL)

AUROHEALTH
NDC 58602-422-12
*Compare to active ingredient
in Children’s ZYRTEC®
Children's
Cetirizine Hydrochloride
Oral Solution USP
1 mg/mL
antihistamine ALLERGY

Indoor &
Outdoor
Allergies

2 yrs &
older
24 Hour
relief of Sneezing Runny Nose

Itchy, Watery Itchy Throat Dye-Free
Eyes or Nose Alcohol-Free
Grape Flavor
4 fl oz (120 mL)
Dosing cup
included